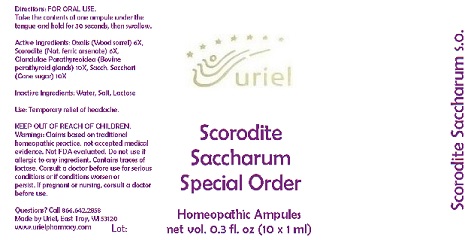 DRUG LABEL: Scorodite Saccharum Special Order
NDC: 48951-8170 | Form: LIQUID
Manufacturer: Uriel Pharmacy Inc.
Category: homeopathic | Type: HUMAN OTC DRUG LABEL
Date: 20170815

ACTIVE INGREDIENTS: BOS TAURUS PARATHYROID GLAND 6 [hp_X]/1 mL; OXALIS ACETOSELLA LEAF 6 [hp_X]/1 mL; FERROUS ARSENATE 6 [hp_X]/1 mL; SUGARCANE 10 [hp_X]/1 mL
INACTIVE INGREDIENTS: WATER; SODIUM CHLORIDE; LACTOSE

Scorodite Saccharum Special Order

INDICATIONS AND USAGE

Directions: FOR ORAL USE.

DOSAGE AND ADMINISTRATION

Take the contents of one ampule under the tongue and hold for 30 seconds, then swallow.

ACTIVE INGREDIENT

Active Ingredients: Oxalis (Wood sorrel) 6X, Scorodite (Nat. ferric arsenate) 6X, Glandulae Parathyreoidea (Bovine parathyroid glands) 10X, Sacch. Sacchari (Cane sugar) 10X

Inactive Ingredients: Water, Salt, Lactose

PURPOSE

Use: Temporary relief of headache.

KEEP OUT OF REACH OF CHILDREN.

WARNINGS

Warnings: Claims based on traditional homeopathic practice, not accepted medical evidence. Not FDA evaluated. Do not use if allergic to any ingredient. Contains traces of lactose. Consult a doctor before use for serious conditions or if conditions worsen or
persist. If pregnant or nursing, consult a doctor before use.

QUESTIONS

Questions? Call 866.642.2858 Made by Uriel, East Troy, WI 53120 www.urielpharmacy.com